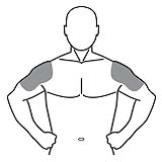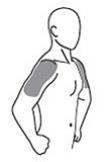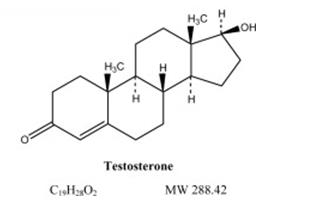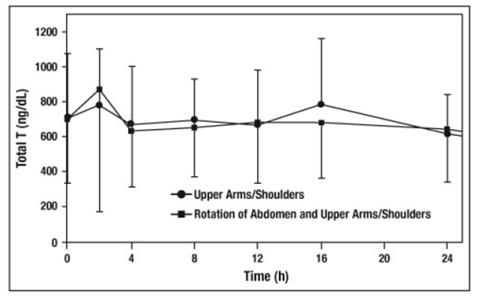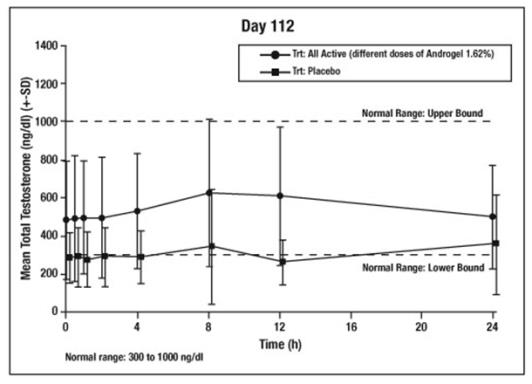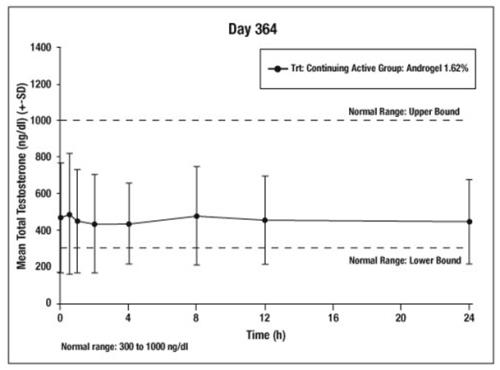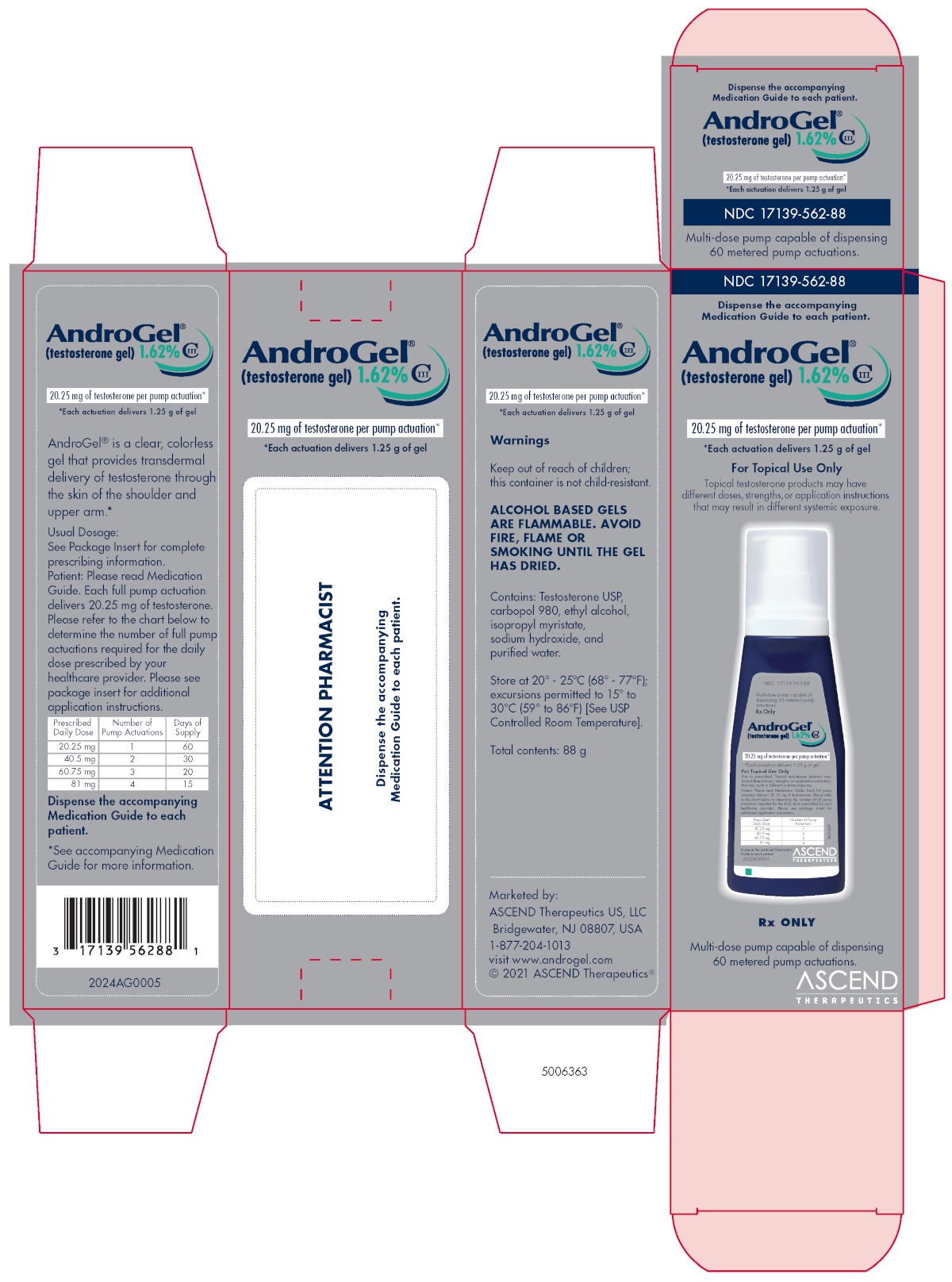 DRUG LABEL: AndroGel
NDC: 17139-562 | Form: GEL
Manufacturer: ASCEND Therapeutics U.S., LLC
Category: prescription | Type: HUMAN PRESCRIPTION DRUG LABEL
Date: 20251022
DEA Schedule: CIII

ACTIVE INGREDIENTS: TESTOSTERONE 16.2 mg/1 g
INACTIVE INGREDIENTS: ALCOHOL; ISOPROPYL MYRISTATE; WATER; SODIUM HYDROXIDE; CARBOMER HOMOPOLYMER TYPE C (ALLYL PENTAERYTHRITOL CROSSLINKED)

HIGHLIGHTS OF PRESCRIBING INFORMATION

These highlights do not include all the information needed to use ANDROGEL 1.62% safely and effectively. See full prescribing information for ANDROGEL 1.62%.
ANDROGEL® (testosterone gel) 1.62% for topical use CIII
Initial U.S. Approval: 1953

WARNING: SECONDARY EXPOSURE TO TESTOSTERONE

See full prescribing information for complete boxed warning.

- Virilization has been reported in children who were secondarily exposed to testosterone gel (5.1, 6.2).
- Children should avoid contact with unwashed or unclothed application sites in men using testosterone gel (2.2, 5.1).
- Healthcare providers should advise patients to strictly adhere to recommended instructions for use (2.2, 5.2, 17).

RECENT MAJOR CHANGES

Warnings and Precautions, Venous Thromboembolism (5.3) 07/2025
Warnings and Precautions, Blood Pressure Increases (5.5) 07/2025
Warnings and Precautions, Cardiovascular Risk (5.5) Removed 07/2025

1 INDICATIONS AND USAGE

AndroGel 1.62% is indicated for replacement therapy in males for conditions associated with a deficiency or absence of endogenous testosterone:

- Primary hypogonadism (congenital or acquired) (1)
- Hypogonadotropic hypogonadism (congenital or acquired) (1)

Limitations of use:

- Safety and efficacy of AndroGel 1.62% in men with “age-related hypogonadism” have not been established. (1)
- Safety and efficacy of AndroGel 1.62% in males less than 18 years old have not been established. (1, 8.4)
- Topical testosterone products may have different doses, strengths, or application instructions that may result in different systemic exposure. (1, 12.3)

2 DOSAGE AND ADMINISTRATION

- Dosage and Administration for AndroGel 1.62% differs from AndroGel 1%. For dosage and administration of AndroGel 1% refer to its full prescribing information. (2)
- Prior to initiating AndroGel 1.62%, confirm the diagnosis of hypogonadism by ensuring that serum testosterone has been measured in the morning on at least two separate days and that these concentrations are below the normal range (2).
- Starting dose of AndroGel 1.62% is 40.5 mg of testosterone (2 pump actuations or a single 40.5 mg packet), applied topically once daily in the morning. (2.1)
- Apply to clean, dry, intact skin of the shoulders and upper arms. Do not apply AndroGel 1.62% to any other parts of the body including the abdomen, genitals, chest, armpits (axillae), or knees. (2.2, 12.3)
  Dose adjustment: AndroGel 1.62% can be dose adjusted between a minimum of 20.25 mg of testosterone (1 pump actuation or a single 20.25 mg packet) and a maximum of 81 mg of testosterone (4 pump actuations or two 40.5 mg packets). The dose should be titrated based on the pre-dose morning serum testosterone concentration at approximately 14 days and 28 days after starting treatment or following dose adjustment. Additionally, serum testosterone concentration should be assessed periodically thereafter. (2.1)
- Patients should wash hands immediately with soap and water after applying AndroGel 1.62% and cover the application site(s) with clothing after the gel has dried. Wash the application site thoroughly with soap and water prior to any situation where skin-to-skin contact of the application site with another person is anticipated. (2.2)

3 DOSAGE FORMS AND STRENGTHS

AndroGel (testosterone gel) 1.62% for topical use is available as follows:

- a metered-dose pump that delivers 20.25 mg testosterone per actuation. (3)
- packets containing 20.25 mg testosterone. (3)
- packets containing 40.5 mg testosterone. (3)

4 CONTRAINDICATIONS

- Men with carcinoma of the breast or known or suspected prostate cancer (4, 5.4)
- Women who are pregnant. Testosterone may cause fetal harm (4, 8.1)

5 WARNINGS AND PRECAUTIONS

- Worsening of Benign Prostatic Hyperplasia (BPH) and Potential Risk of Prostate Cancer: Monitor patients with benign prostatic hyperplasia (BPH) for worsening of signs and symptoms of BPH. (5.4)
- Potential for Secondary Exposure to Testosterone: Avoid unintentional exposure of women or children to AndroGel 1.62%. Secondary exposure to testosterone can produce signs of virilization. AndroGel 1.62% should be discontinued until the cause of virilization is identified (5.1)
- Venous Thromboembolism (VTE): VTE including deep vein thrombosis (DVT) and pulmonary embolism (PE) have been reported in patients using testosterone products. Evaluate patients with signs or symptoms consistent with DVT or PE. (5.3)
- Blood Pressure Increases: AndroGel 1.62% can increase blood pressure, which can increase cardiovascular risk over time. Measure blood pressure periodically. Not recommended for use in men with uncontrolled hypertension (5.5)
- Potential for Adverse Effects on Spermatogenesis: Exogenous administration of androgens may lead to azoospermia (5.8)
- Edema: Edema with or without congestive heart failure (CHF) may be a complication in patients with preexisting cardiac, renal, or hepatic disease (5.10, 6.2)
- Sleep Apnea: Sleep apnea may occur in those with risk factors (5.12)
- Monitor serum testosterone, prostate specific antigen (PSA), hemoglobin, hematocrit, liver function tests and lipid concentrations periodically (5.1, 5.2, 5.9, 5.13)
- Flammability: AndroGel 1.62% is flammable until dry (5.16)

6 ADVERSE REACTIONS

The most common adverse reaction (incidence ≥ 5%) is an increase in prostate specific antigen (PSA). (6.1)

To report SUSPECTED ADVERSE REACTIONS, contact ASCEND Therapeutics US, LLC at 1-877-204-1013 or FDA at 1-800-FDA-1088 or www.fda.gov/medwatch.

7 DRUG INTERACTIONS

- Androgens may decrease blood glucose and therefore may decrease insulin requirements in diabetic patients (7.1)
- Changes in anticoagulant activity may be seen with androgens. More frequent monitoring of International Normalized Ratio (INR) and prothrombin time is recommended (7.2)
- Use of testosterone with adrenocorticotrophic hormone (ACTH) or corticosteroids may result in increased fluid retention. Use with caution, particularly in patients with cardiac, renal, or hepatic disease (7.3)

8 USE IN SPECIFIC POPULATIONS

There are insufficient long-term safety data in geriatric patients using AndroGel 1.62% to assess the potential risks of cardiovascular disease and prostate cancer. (8.5)

FULL PRESCRIBING INFORMATION

WARNING: SECONDARY EXPOSURE TO TESTOSTERONE

- Virilization has been reported in children who were secondarily exposed to testosterone gel [see Warnings and Precautions (5.1) and Adverse Reactions (6.2)].
- Children should avoid contact with unwashed or unclothed application sites in men using testosterone gel [see Dosage and Administration (2.2) and Warnings and Precautions (5.1)].
- Healthcare providers should advise patients to strictly adhere to recommended instructions for use [see Dosage and Administration (2.2), Warnings and Precautions (5.1) and Patient Counseling Information (17)].

1 INDICATIONS AND USAGE

AndroGel 1.62% is indicated for replacement therapy in adult males for conditions associated with a deficiency or absence of endogenous testosterone:

- Primary hypogonadism (congenital or acquired): testicular failure due to conditions such as cryptorchidism, bilateral torsion, orchitis, vanishing testis syndrome, orchiectomy, Klinefelter's syndrome, chemotherapy, or toxic damage from alcohol or heavy metals. These men usually have low serum testosterone concentrations and gonadotropins (follicle-stimulating hormone [FSH], luteinizing hormone [LH]) above the normal range.
- Hypogonadotropic hypogonadism (congenital or acquired): gonadotropin or luteinizing hormone-releasing hormone (LHRH) deficiency or pituitary-hypothalamic injury from tumors, trauma, or radiation. These men have low testosterone serum concentrations, but have gonadotropins in the normal or low range.

Limitations of use:

- Safety and efficacy of AndroGel 1.62% in men with “age-related hypogonadism” (also referred to as “late-onset hypogonadism”) have not been established.
- Safety and efficacy of AndroGel 1.62% in males less than 18 years old have not been established [see Use in Specific Populations (8.4)].
- Topical testosterone products may have different doses, strengths, or application instructions that may result in different systemic exposure [see Indications and Usage (1), and Clinical Pharmacology (12.3)].

2 DOSAGE AND ADMINISTRATION

Dosage and Administration for AndroGel 1.62% differs from AndroGel 1%. For dosage and administration of AndroGel 1% refer to its full prescribing information. (2)

Prior to initiating AndroGel 1.62%, confirm the diagnosis of hypogonadism by ensuring that serum testosterone concentrations have been measured in the morning on at least two separate days and that these serum testosterone concentrations are below the normal range.

2.1 Dosing and Dose Adjustment

The recommended starting dose of AndroGel 1.62% is 40.5 mg of testosterone (2 pump actuations or a single 40.5 mg packet) applied topically once daily in the morning to the shoulders and upper arms.

The dose can be adjusted between a minimum of 20.25 mg of testosterone (1 pump actuation or a single 20.25 mg packet) and a maximum of 81 mg of testosterone (4 pump actuations or two 40.5 mg packets). To ensure proper dosing, the dose should be titrated based on the pre-dose morning serum testosterone concentration from a single blood draw at approximately 14 days and 28 days after starting treatment or following dose adjustment. In addition, serum testosterone concentration should be assessed periodically thereafter. Table 1 describes the dose adjustments required at each titration step.

Table 1: Dose Adjustment Criteria
Pre-Dose Morning Total Serum Testosterone Concentration | Dose Titration
Greater than 750 ng/dL | Decrease daily dose by 20.25 mg (1 pump actuation or the equivalent of one 20.25 mg packet)
Equal to or greater than 350 and equal to or less than 750 ng/dL | No change: continue on current dose
Less than 350 ng/dL | Increase daily dose by 20.25 mg (1 pump actuation or the equivalent of one 20.25 mg packet)

The application site and dose of AndroGel 1.62% are not substitutable with other topical testosterone products.

2.2 Administration Instructions

AndroGel 1.62% should be applied to clean, dry, intact skin of the upper arms and shoulders. Do not apply AndroGel 1.62% to any other parts of the body, including the abdomen, genitals, chest, armpits (axillae), or knees [see Clinical Pharmacology (12.3)]. Area of application should be limited to the area that will be covered by the patient's short sleeve t-shirt. Patients should be instructed to use the palm of the hand to apply AndroGel 1.62% and spread across the maximum surface area as directed in Table 2 (for pump) and Table 3 (for packets) and in Figure 1.

Table 2: Application Sites for AndroGel 1.62%, Pump
Total Dose of Testosterone | Total Pump Actuations | Pump Actuations Per Upper Arm and Shoulder
 |  | Upper Arm and Shoulder #1 | Upper Arm and Shoulder #2
20.25 mg | 1 | 1 | 0
40.5 mg | 2 | 1 | 1
60.75 mg | 3 | 2 | 1
81 mg | 4 | 2 | 2

Table 3: Application Sites for AndroGel 1.62%, Packets
Total Dose of Testosterone | Total packets | Gel Applications Per Upper Arm and Shoulder
 |  | Upper Arm and Shoulder #1 | Upper Arm and Shoulder #2
20.25 mg | One 20.25 mg packet | One 20.25 mg packet | 0
40.5 mg | One 40.5 mg packet | Half of contents of One 40.5 mg packet | Half of contents of One 40.5 mg packet
60.75 mg | One 20.25 mg packet AND One 40.5 mg packet | One 40.5 mg packet | One 20.25 mg packet
81 mg | Two 40.5 mg packets | One 40.5 mg packet | One 40.5 mg packet

The prescribed daily dose of AndroGel 1.62% should be applied to the right and left upper arms and shoulders as shown in the shaded areas in Figure 1.

Figure 1. Application Sites for AndroGel 1.62%

Once the application site is dry, the site should be covered with clothing [see Clinical Pharmacology (12.3)]. Wash hands thoroughly with soap and water. Avoid fire, flames or smoking until the gel has dried since alcohol based products, including AndroGel 1.62%, are flammable.

The patient should avoid swimming or showering or washing the administration site for a minimum of 2 hours after application [see Clinical Pharmacology (12.3)].

To obtain a full first dose, it is necessary to prime the canister pump. To do so, with the canister in the upright position, slowly and fully depress the actuator three times. Safely discard the gel from the first three actuations. It is only necessary to prime the pump before the first dose.

After the priming procedure, fully depress the actuator once for every 20.25 mg of AndroGel 1.62%. AndroGel 1.62% should be delivered directly into the palm of the hand and then applied to the application sites.

When using packets, the entire contents should be squeezed into the palm of the hand and immediately applied to the application sites. When 40.5 mg packets need to be split between the left and right shoulder, patients may squeeze a portion of the gel from the packet into the palm of the hand and apply to application sites. Repeat until entire contents have been applied. Alternatively, AndroGel 1.62% can be applied directly to the application sites from the pump or packets.

Strict adherence to the following precautions is advised in order to minimize the potential for secondary exposure to testosterone from AndroGel 1.62%-treated skin:

- Children and women should avoid contact with unwashed or unclothed application site(s) of men using AndroGel 1.62%.
- AndroGel 1.62% should only be applied to the upper arms and shoulders. The area of application should be limited to the area that will be covered by a short sleeve t-shirt.
- Patients should wash their hands with soap and water immediately after applying AndroGel 1.62%.
- Patients should cover the application site(s) with clothing (e.g., a t-shirt) after the gel has dried.
- Prior to situations in which direct skin-to-skin contact is anticipated, patients should wash the application site(s) thoroughly with soap and water to remove any testosterone residue.
- In the event that unwashed or unclothed skin to which AndroGel 1.62% has been applied comes in direct contact with the skin of another person, the general area of contact on the other person should be washed with soap and water as soon as possible.

3 DOSAGE FORMS AND STRENGTHS

AndroGel (testosterone gel) 1.62% for topical use only, is available as follows:

- A metered-dose pump. Each pump actuation delivers 20.25 mg of testosterone in 1.25 g of gel.
- A unit dose packet containing 20.25 mg of testosterone in 1.25 g of gel.
- A unit dose packet containing 40.5 mg of testosterone in 2.5 g of gel.

4 CONTRAINDICATIONS

- AndroGel 1.62% is contraindicated in men with carcinoma of the breast or known or suspected carcinoma of the prostate [see Warnings and Precautions (5.4) and Adverse Reactions (6.1)].
- AndroGel 1.62% is contraindicated in women who are pregnant. AndroGel 1.62% can cause virilization of the female fetus when administered to a pregnant woman. Pregnant women need to be aware of the potential for transfer of testosterone from men treated with AndroGel 1.62%. If a pregnant woman is exposed to AndroGel 1.62%, she should be apprised of the potential hazard to the fetus [see Warnings and Precautions (5.1) and Use in Specific Populations (8.1)].

5 WARNINGS AND PRECAUTIONS

5.1 Potential for Secondary Exposure to Testosterone

Cases of secondary exposure resulting in virilization of children have been reported in postmarketing surveillance. Signs and symptoms have included enlargement of the penis or clitoris, development of pubic hair, increased erections and libido, aggressive behavior, and advanced bone age. In most cases, these signs and symptoms regressed with removal of the exposure to testosterone gel. In a few cases, however, enlarged genitalia did not fully return to age-appropriate normal size, and bone age remained modestly greater than chronological age. The risk of transfer was increased in some of these cases by not adhering to precautions for the appropriate use of the topical testosterone product. Children and women should avoid contact with unwashed or unclothed application sites in men using AndroGel 1.62% [see Dosage and Administration (2.2), Use in Specific Populations (8.1) and Clinical Pharmacology (12.3)].

Inappropriate changes in genital size or development of pubic hair or libido in children, or changes in body hair distribution, significant increase in acne, or other signs of virilization in adult women should be brought to the attention of a physician and the possibility of secondary exposure to testosterone gel should also be brought to the attention of a physician. Testosterone gel should be promptly discontinued until the cause of virilization has been identified.

5.2 Polycythemia

Increases in hematocrit, reflective of increases in red blood cell mass, may require lowering or discontinuation of testosterone. Check hematocrit prior to initiating treatment. It would also be appropriate to re-evaluate the hematocrit 3 to 6 months after starting treatment, and then annually. If hematocrit becomes elevated, stop therapy until hematocrit decreases to an acceptable concentration. An increase in red blood cell mass may increase the risk of thromboembolic events.

5.3 Venous Thromboembolism

There have been postmarketing reports of venous thromboembolic events (VTE), including deep vein thrombosis (DVT) and pulmonary embolism (PE), in patients using testosterone products such as AndroGel 1.62%.

In the Testosterone Replacement therapy for Assessment of long-term Vascular Events and efficacy ResponSE in hypogonadal men (TRAVERSE) Study, a randomized, double-blind, placebo-controlled, cardiovascular (CV) outcomes study, compared to placebo, AndroGel 1.62% was associated with a numerically higher incidence of VTE (1.7% vs 1.2%) which included DVT (0.6% vs 0.5%) and PE events (0.9% vs 0.5%) [see Adverse Reactions (6.1)].

Evaluate patients who report symptoms of pain, edema, warmth and erythema in the lower extremity for DVT and those who present with acute shortness of breath for PE. If a venous thromboembolic event is suspected, discontinue treatment with AndroGel 1.62% and initiate appropriate workup and management [see Adverse Reactions (6.2)].

5.4 Worsening of Benign Prostatic Hyperplasia (BPH) and Potential Risk of Prostate Cancer

- Patients with BPH treated with androgens are at an increased risk for worsening of signs and symptoms of BPH. Monitor patients with BPH for worsening signs and symptoms.
- Patients treated with androgens may be at increased risk for prostate cancer. Evaluate patients for prostate cancer prior to initiating and during treatment with androgens [see Contraindications (4), Adverse Reactions (6.1) and Nonclinical Toxicology (13.1)].

5.5 Blood Pressure Increases

AndroGel 1.62% can increase blood pressure. In an ambulatory blood pressure monitoring (ABPM) study, Androgel 1.62% increased the mean systolic/diastolic blood pressure by 1.9/1.3 mm Hg from baseline after 16 weeks of treatment. In patients with hypertension on antihypertensive therapy, AndroGel 1.62% increased the mean systolic/diastolic BP by 3.0/2.2 mm Hg from baseline. Blood pressure increases can increase cardiovascular (CV) risk over time.

The CV risk associated with Androgel 1.62% was evaluated in TRAVERSE, a randomized, double-blind, placebo-controlled, CV outcomes study in men with a history of CV disease or multiple CV risk factors. In TRAVERSE, mean systolic blood pressure in the group treated with Androgel 1.62% increased by 1.0 mm Hg from baseline to 36 months, whereas a mean decrease from baseline of 0.5 mm Hg was observed in the placebo group at this timepoint, for a mean between-group difference of 1.5 mm Hg. However, the incidences of major adverse cardiovascular events (MACE), including cardiovascular death, non-fatal myocardial infarction [MI] and non-fatal stroke, were similar between treatment groups (7% for Androgel 1.62% vs 7.3% for placebo) [See Adverse Reactions (6.1)].

Monitor blood pressure periodically in men using Androgel 1.62%, especially men with hypertension. Androgel 1.62% is not recommended for use in patients with uncontrolled hypertension.

5.6 Abuse of Testosterone and Monitoring of Serum Testosterone Concentrations

Testosterone has been subject to abuse, typically at doses higher than recommended for the approved indication and in combination with other anabolic androgenic steroids. Anabolic androgenic steroid abuse can lead to serious cardiovascular and psychiatric adverse reactions [see Drug Abuse and Dependence (9)].

If testosterone abuse is suspected, check serum testosterone concentrations to ensure they are within therapeutic range. However, testosterone levels may be in the normal or subnormal range in men abusing synthetic testosterone derivatives. Counsel patients concerning the serious adverse reactions associated with abuse of testosterone and anabolic androgenic steroids. Conversely, consider the possibility of testosterone and anabolic androgenic steroid abuse in suspected patients who present with serious cardiovascular or psychiatric adverse events.

5.7 Not for Use in Women

Due to the lack of controlled evaluations in women and potential virilizing effects, AndroGel 1.62% is not indicated for use in women [see Contraindications (4) and Use in Specific Populations (8.1, 8.2)].

5.8 Potential for Adverse Effects on Spermatogenesis

With large doses of exogenous androgens, including AndroGel 1.62%, spermatogenesis may be suppressed through feedback inhibition of pituitary FSH possibly leading to adverse effects on semen parameters including sperm count.

5.9 Hepatic Adverse Effects

Prolonged use of high doses of orally active 17-alpha-alkyl androgens (e.g., methyltestosterone) has been associated with serious hepatic adverse effects (peliosis hepatis, hepatic neoplasms, cholestatic hepatitis, and jaundice). Peliosis hepatis can be a life-threatening or fatal complication. Long-term therapy with intramuscular testosterone enanthate has produced multiple hepatic adenomas. AndroGel 1.62% is not known to cause these adverse effects.

5.10 Edema

Androgens, including AndroGel 1.62%, may promote retention of sodium and water. Edema, with or without congestive heart failure, may be a serious complication in patients with preexisting cardiac, renal, or hepatic disease [see Adverse Reactions (6.2)].

5.11 Gynecomastia

Gynecomastia may develop and persist in patients being treated with androgens, including AndroGel 1.62%, for hypogonadism.

5.12 Sleep Apnea

The treatment of hypogonadal men with testosterone may potentiate sleep apnea in some patients, especially those with risk factors such as obesity or chronic lung diseases.

5.13 Lipid Changes

Changes in serum lipid profile may require dose adjustment or discontinuation of testosterone therapy, such as AndroGel 1.62%. Monitor the lipid profile periodically, particularly after starting testosterone therapy.

5.14 Hypercalcemia

Androgens, including AndroGel 1.62 %, should be used with caution in cancer patients at risk of hypercalcemia (and associated hypercalciuria). Regular monitoring of serum calcium concentrations is recommended in these patients.

5.15 Decreased Thyroxine-binding Globulin

Androgens, including AndroGel 1.62%, may decrease concentrations of thyroxin-binding globulins, resulting in decreased total T4 serum concentrations and increased resin uptake of T3 and T4. Free thyroid hormone concentrations remain unchanged, however, and there is no clinical evidence of thyroid dysfunction.

5.16 Flammability

Alcohol based products, including AndroGel 1.62%, are flammable; therefore, patients should be advised to avoid fire, flame or smoking until the AndroGel 1.62% has dried.

6 ADVERSE REACTIONS

6.1 Clinical Trial Experience

Because clinical trials are conducted under widely varying conditions, adverse reaction rates observed in the clinical trials of a drug cannot be directly compared to rates in the clinical trials of another drug and may not reflect the rates observed in practice.

AndroGel 1.62% was evaluated in a two-phase, 364-day, controlled clinical study. The first phase was a multi-center, randomized, double-blind, parallel-group, placebo-controlled period of 182 days, in which 234 hypogonadal men were treated with AndroGel 1.62% and 40 received placebo. Patients could continue in an open-label, non-comparative, maintenance period for an additional 182 days [see Clinical Studies (14.1)].

The most common adverse reaction reported in the double-blind period was increased prostate specific antigen (PSA) reported in 26 AndroGel 1.62%-treated patients (11.1%). In 17 patients, increased PSA was considered an adverse event by meeting one of the two pre-specified criteria for abnormal PSA values, defined as (1) average serum PSA >4 ng/mL based on two separate determinations, or (2) an average change from baseline in serum PSA of greater than 0.75 ng/mL on two determinations.

During the 182-day, double-blind period of the clinical trial, the mean change in serum PSA value was 0.14 ng/mL for patients receiving AndroGel 1.62% and -0.12 ng/mL for the patients in the placebo group. During the double-blind period, seven patients had a PSA value >4.0 ng/mL, four of these seven patients had PSA less than or equal to 4.0 ng/mL upon repeat testing. The other three patients did not undergo repeat PSA testing.

During the 182-day, open-label period of the study, the mean change in serum PSA values was 0.10 ng/mL for both patients continuing on active therapy and patients transitioning onto active from placebo. During the open-label period, three patients had a serum PSA value > 4.0 ng/mL, two of whom had a serum PSA less than or equal to 4.0 ng/mL upon repeated testing. The other patient did not undergo repeat PSA testing. Among previous placebo patients, 3 of 28 (10.7%), had increased PSA as an adverse event in the open-label period.

Table 4 shows adverse reactions reported by >2% of patients in the 182-day, double-blind period of the AndroGel 1.62% clinical trial and more frequent in the AndroGel 1.62% treated group versus placebo.

Table 4: Adverse Reactions Reported in >2% of Patients in the 182-Day, Double-Blind Period of AndroGel 1.62% Clinical Trial
 | Number (%) of Patients
Adverse Reaction | AndroGel 1.62% N=234 | Placebo N=40
PSA increased* | 26 (11.1%) | 0%
Emotional lability** | 6 (2.6%) | 0%
Hypertension | 5 (2.1%) | 0%
Hematocrit or hemoglobin increased | 5 (2.1%) | 0%
Contact dermatitis*** | 5 (2.1%) | 0%
* PSA increased includes: PSA values that met pre-specified criteria for abnormal PSA values (an average change from baseline > 0.75 ng/mL and/or an average PSA value >4.0 ng/mL based on two measurements) as well as those reported as adverse events.
** Emotional lability includes: mood swings, affective disorder, impatience, anger, and aggression.
*** Contact dermatitis includes: 4 patients with dermatitis at non-application sites.

Other adverse reactions occurring in less than or equal to 2% of AndroGel 1.62%-treated patients and more frequently than placebo included: frequent urination, and hyperlipidemia.

In the open-label period of the study (N=191), the most commonly reported adverse reaction (experienced by greater than 2% of patients) was increased PSA (n=13; 6.2%) and sinusitis. Other adverse reactions reported by less than or equal to 2% of patients included increased hemoglobin or hematocrit, hypertension, acne, libido decreased, insomnia, and benign prostatic hypertrophy.

During the 182-day, double-blind period of the clinical trial, 25 AndroGel 1.62%-treated patients (10.7%) discontinued treatment because of adverse reactions. These adverse reactions included 17 patients with PSA increased and 1 report each of: hematocrit increased, blood pressure increased, frequent urination, diarrhea, fatigue, pituitary tumor, dizziness, skin erythema and skin nodule (same patient – neither at application site), vasovagal syncope, and diabetes mellitus. During the 182-day, open-label period, 9 patients discontinued treatment because of adverse reactions. These adverse reactions included 6 reports of PSA increased, 2 of hematocrit increased, and 1 each of triglycerides increased and prostate cancer.

Application Site Reactions

In the 182-day double-blind period of the study, application site reactions were reported in two (2/234; 0.9%) patients receiving AndroGel 1.62%, both of which resolved. Neither of these patients discontinued the study due to application site adverse reactions. In the open-label period of the study, application site reactions were reported in three (3/219; 1.4%) additional patients that were treated with AndroGel 1.62%. None of these subjects were discontinued from the study due to application site reactions.

Blood Pressure Increases

In a 4-month clinical study, 24-hour ambulatory blood pressure monitoring (ABPM) was conducted on 246 patients. ABPM was conducted at baseline and at Week 16 of AndroGel 1.62% therapy. A total of 169 patients had acceptable ABPM recordings at both baseline and Week 16 and were at least 85% compliant with study drug. In that group, the mean change in 24-hour systolic blood pressure (BP) and diastolic BP from baseline to end-of-treatment at Week 16 (n=169) was 1.9 mm Hg (95% CI 0.6, 3.1) and 1.3 mm Hg (95% CI 0.5, 2.1), respectively. In patients with a history of hypertension who were receiving antihypertensive therapy, the mean ABPM systolic and diastolic BP increased by 3.0 mm Hg [95% CI 0.8, 5.2] and 2.2 mm Hg [95% CI 0.8, 3.5], respectively [n=72]). In patients with no history of hypertension, the mean systolic and diastolic blood pressure increased by 1.2 mm Hg [95% CI -0.2, 2.7] and 0.9 mm Hg [95% CI -0.1, 1.8], respectively [n=91].

Four patients (2.8 %) on AndroGel 1.62%, all of whom were receiving antihypertensive medications at baseline, either started new antihypertensive medications (n=2) or had their antihypertensive medication regimen adjusted (n=2) during the ABPM study.

Of the 246 patients in the ABPM study who used AndroGel 1.62%, 10 patients (4.1%) were reported to have either an adverse reaction of hypertension (5 patients, 2.0%) or increased blood pressure (5 patients, 2.0%).

Cardiovascular Outcomes

TRAVERSE was a randomized, double-blind, cardiovascular outcomes study to assess the cardiovascular (CV) safety of Androgel 1.62% compared to placebo in 5198 hypogonadal men aged 45 to 80 years with a history of CV disease or with multiple CV risk factors. The primary outcome was the incidence of the composite endpoint of major adverse cardiovascular events (MACE), consisting of CV death, non-fatal myocardial infarction (MI), and non-fatal stroke.

The mean duration of therapy was approximately 22 months. The mean duration of follow-up was 33 months. Approximately 61% of all patients discontinued AndroGel 1.62% or placebo therapy. The mean (±SD) daily dose of testosterone was 65±22 mg.

The mean patient age (±SD) was 63.3 (7.9) years, with 2452 patients aged 65 years or more (47%); 2847 (about 55%) patients had pre-existing cardiovascular disease, whereas 2357 (about 45%) patients had an elevated cardiovascular risk at baseline, and mean BMI was 35kg/m^2. Approximately 80% of patients were White, 17% were Black, and 3% were of other races or ethnic groups. Approximately 69%, 84%, and 93% had diabetes mellitus, hyperlipidemia, and hypertension, respectively.

The mean serum testosterone concentration at baseline in patients receiving AndroGel 1.62% was 220.4 ng/dL (n=2596). The mean serum testosterone concentrations at 12 months, 24 months, 36 months, and 48 months in patients receiving AndroGel 1.62% were 440.5 ng/dL (n=1683), 420.9 ng/dl (n=1125), 428.7 ng/dL (n=731), and 365.2 ng/dL (n=220), respectively.

For patients treated with AndroGel 1.62%, the incidence of MACE was 7.0% (n=182 events) and for those receiving placebo, the incidence of MACE was 7.3% (n=190 events). The study demonstrated non-inferiority of AndroGel 1.62% versus placebo because the upper bound of 95% CI was less than the pre-specified risk margin, of 1.5 for MACE (Hazard Ratio 0.96 [95% CI: 0.78, 1.17]).

Additional Adverse Reactions Reported in TRAVERSE

Additional adverse reactions reported in TRAVERSE at an incidence rate >2% in either treatment group and greater in AndroGel 1.62% versus placebo included: nonfatal arrythmias warranting intervention (5.2% vs 3.3%), atrial fibrillation (3.5% vs 2.4%), acute kidney injury (2.3% vs 1.5%) and bone fracture (3.5% vs 2.5%). For the adverse reaction of bone fracture, each event was adjudicated by clinical review.

6.2 Postmarketing Experience

The following adverse reactions have been identified during post approval use of AndroGel 1.62%. Because the reactions are reported voluntarily from a population of uncertain size, it is not always possible to reliably estimate their frequency or establish a causal relationship to drug exposure (Table 5).

Table 5: Adverse Reactions from Post Approval Experience of AndroGel 1.62% by System Organ Class
System Organ Class | Adverse Reaction
Blood and lymphatic system disorders: | Elevated hemoglobin or hematocrit, polycythemia, anemia
Cardiovascular disorders: | Myocardial infarction, stroke
Endocrine disorders: | Hirsutism
Gastrointestinal disorders: | Nausea
General disorders: | Asthenia, edema, malaise
Genitourinary disorders: | Impaired urination*
Hepatobiliary disorders: | Abnormal liver function tests
Investigations: | Lab test abnormal**, elevated PSA, electrolyte changes (nitrogen, calcium, potassium [includes hypokalemia] , phosphorus, sodium), impaired glucose tolerance, hyperlipidemia, HDL, fluctuating testosterone levels, weight increase
Neoplasms: | Prostate cancer
Nervous system disorders: | Dizziness, headache, insomnia, sleep apnea
Psychiatric disorders: | Amnesia, anxiety, depression, hostility, emotional lability, decreased libido, nervousness
Reproductive system and breast disorders: | Gynecomastia, mastodynia, oligospermia, priapism (frequent or prolonged erections), prostate enlargement, BPH, testis disorder***
Respiratory disorders: | Dyspnea
Skin and subcutaneous tissue disorders: | Acne, alopecia, application site reaction (discolored hair, dry skin, erythema, paresthesia, pruritus, rash), skin dry, pruritus, sweating
Vascular disorders: | Hypertension, vasodilation (hot flushes), venous thromboembolism
* Impaired urination includes nocturia, urinary hesitancy, urinary incontinence, urinary retention, urinary urgency and weak urinary stream
**Lab test abnormal includes elevated AST, elevated ALT, elevated testosterone, elevated hemoglobin or hematocrit, elevated cholesterol, elevated cholesterol/LDL ratio, elevated triglycerides, or elevated serum creatinine
***Testis disorder includes atrophy or non-palpable testis, varicocele, testis sensitivity or tenderness

Secondary Exposure to Testosterone in Children

Cases of secondary exposure to testosterone resulting in virilization of children have been reported in postmarketing surveillance of testosterone gel products. Signs and symptoms of these reported cases have included enlargement of the clitoris (with surgical intervention) or the penis, development of pubic hair, increased erections and libido, aggressive behavior, and advanced bone age. In most cases with a reported outcome, these signs and symptoms were reported to have regressed with removal of the testosterone gel exposure. In a few cases, however, enlarged genitalia did not fully return to age appropriate normal size, and bone age remained modestly greater than chronological age. In some of the cases, direct contact with the sites of application on the skin of men using testosterone gel was reported. In at least one reported case, the reporter considered the possibility of secondary exposure from items such as the testosterone gel user's shirts and/or other fabric, such as towels and sheets [see Warnings and Precautions (5.1)].

7 DRUG INTERACTIONS

7.1 Insulin

Changes in insulin sensitivity or glycemic control may occur in patients treated with androgens. In diabetic patients, the metabolic effects of androgens may decrease blood glucose and, therefore, may decrease insulin requirements.

7.2 Oral Anticoagulants

Changes in anticoagulant activity may be seen with androgens, therefore more frequent monitoring of international normalized ratio (INR) and prothrombin time are recommended in patients taking anticoagulants, especially at the initiation and termination of androgen therapy.

7.3 Corticosteroids

The concurrent use of testosterone with adrenocorticotropic hormone (ACTH) or corticosteroids may result in increased fluid retention and requires careful monitoring particularly in patients with cardiac, renal or hepatic disease.

8 USE IN SPECIFIC POPULATIONS

8.1 Pregnancy

Risk Summary

AndroGel 1.62% is contraindicated in pregnant women. Testosterone is teratogenic and may cause fetal harm when administered to a pregnant woman based on data from animal studies and its mechanism of action [see Contraindications (4) and Clinical Pharmacology (12.1)]. Exposure of a female fetus to androgens may result in varying degrees of virilization. In animal developmental studies, exposure to testosterone in utero resulted in hormonal and behavioral changes in offspring and structural impairments of reproductive tissues in female and male offspring. These studies did not meet current standards for nonclinical development toxicity studies.

Data

Animal Data

In developmental studies conducted in rats, rabbits, pigs, sheep and rhesus monkeys, pregnant animals received intramuscular injection of testosterone during the period of organogenesis. Testosterone treatment at doses that were comparable to those used for testosterone replacement therapy resulted in structural impairments in both female and male offspring. Structural impairments observed in females included increased ano-genital distance, phallus development, empty scrotum, no external vagina, intrauterine growth retardation, reduced ovarian reserve, and increased ovarian follicular recruitment. Structural impairments seen in male offspring included increased testicular weight, larger seminal tubular lumen diameter, and higher frequency of occluded tubule lumen. Increased pituitary weight was seen in both sexes.

Testosterone exposure in utero also resulted in hormonal and behavioral changes in offspring. Hypertension was observed in pregnant female rats and their offspring exposed to doses approximately twice those used for testosterone replacement therapy.

8.2 Lactation

Risk Summary

AndroGel 1.62% is not indicated for use in women.

8.3 Females and Males of Reproductive Potential

Infertility

Testis disorder, testicular atrophy, and oligospermia have been identified during use of AndroGel 1.62% [see Adverse Reactions (6.1, 6.2)].

During treatment with large doses of exogenous androgens, including AndroGel 1.62%, spermatogenesis may be suppressed through feedback inhibition of the hypothalamic-pituitary-testicular axis [see Warnings and Precautions (5.8)]. Reduced fertility is observed in some men taking testosterone replacement therapy. Testicular atrophy, subfertility, and infertility have also been reported in men who abuse anabolic androgenic steroids [see Drug Abuse and Dependence (9.2)]. With either type of use, the impact on fertility may be irreversible.

8.4 Pediatric Use

The safety and effectiveness of AndroGel 1.62% in pediatric patients less than 18 years old has not been established. Improper use may result in acceleration of bone age and premature closure of epiphyses.

8.5 Geriatric Use

There have not been sufficient numbers of geriatric patients involved in controlled clinical studies utilizing AndroGel 1.62% to determine whether efficacy in those over 65 years of age differs from younger subjects. Of the 234 patients enrolled in the clinical trial utilizing AndroGel 1.62%, 21 were over 65 years of age. Additionally, there is insufficient long-term safety data in geriatric patients to assess the potentially increased risks of cardiovascular disease and prostate cancer.

Geriatric patients treated with androgens may also be at risk for worsening of signs and symptoms of BPH.

8.6 Renal Impairment

No studies were conducted involving patients with renal impairment.

8.7 Hepatic Impairment

No studies were conducted in patients with hepatic impairment.

9 DRUG ABUSE AND DEPENDENCE

9.1 Controlled Substance

AndroGel 1.62% contains testosterone, a Schedule III controlled substance in the Controlled Substances Act.

9.2 Abuse

Drug abuse is intentional non-therapeutic use of a drug, even once, for its rewarding psychological and physiological effects. Abuse and misuse of testosterone are seen in male and female adults and adolescents. Testosterone, often in combination with other anabolic androgenic steroids (AAS), and not obtained by prescription through a pharmacy, may be abused by athletes and bodybuilders. There have been reports of misuse by men taking higher doses of legally obtained testosterone than prescribed and continuing testosterone despite adverse events or against medical advice.

Abuse-Related Adverse Reactions

Serious adverse reactions have been reported in individuals who abuse anabolic androgenic steroids and include cardiac arrest, myocardial infarction, hypertrophic cardiomyopathy, congestive heart failure, cerebrovascular accident, hepatotoxicity, and serious psychiatric manifestations, including major depression, mania, paranoia, psychosis, delusions, hallucinations, hostility and aggression.

The following adverse reactions have also been reported in men: transient ischemic attacks, convulsions, hypomania, irritability, dyslipidemias, testicular atrophy, subfertility, and infertility.

The following additional adverse reactions have been reported in women: hirsutism, virilization, deepening of voice, clitoral enlargement, breast atrophy, male-pattern baldness, and menstrual irregularities.

The following adverse reactions have been reported in male and female adolescents: premature closure of bony epiphyses with termination of growth, and precocious puberty.

Because these reactions are reported voluntarily from a population of uncertain size and may include abuse of other agents, it is not always possible to reliably estimate their frequency or establish a causal relationship to drug exposure.

9.3 Dependence

Behaviors Associated with Addiction

Continued abuse of testosterone and other anabolic steroids, leading to addiction is characterized by the following behaviors:

- Taking greater dosages than prescribed
- Continued drug use despite medical and social problems due to drug use
- Spending significant time to obtain the drug when supplies of the drug are interrupted
- Giving a higher priority to drug use than other obligations
- Having difficulty in discontinuing the drug despite desires and attempts to do so
- Experiencing withdrawal symptoms upon abrupt discontinuation of use

Physical dependence is characterized by withdrawal symptoms after abrupt drug discontinuation or a significant dose reduction of a drug. Individuals taking supratherapeutic doses of testosterone may experience withdrawal symptoms lasting for weeks or months which include depressed mood, major depression, fatigue, craving, restlessness, irritability, anorexia, insomnia, decreased libido and hypogonadotropic hypogonadism.

Drug dependence in individuals using approved doses of testosterone for approved indications has not been documented.

10 OVERDOSAGE

There is a single report of acute overdosage after parenteral administration of an approved testosterone product in the literature. This subject had serum testosterone concentrations of up to 11,400 ng/dL, which were implicated in a cerebrovascular accident. There were no reports of overdosage in the AndroGel 1.62% clinical trial.

Treatment of overdosage would consist of discontinuation of AndroGel 1.62%, washing the application site with soap and water, and appropriate symptomatic and supportive care.

11 DESCRIPTION

AndroGel (testosterone gel) 1.62% for topical use is a clear, colorless gel containing testosterone. Testosterone is an androgen. AndroGel 1.62% is available in a metered-dose pump or unit dose packets.

The active pharmacologic ingredient in AndroGel 1.62% is testosterone. Testosterone USP is a white to almost white powder chemically described as 17-beta hydroxyandrost-4-en-3-one. The structural formula is:

The inactive ingredients in AndroGel 1.62% are: carbopol 980, ethyl alcohol, isopropyl myristate, purified water, and sodium hydroxide.

12 CLINICAL PHARMACOLOGY

12.1 Mechanism of Action

Endogenous androgens, including testosterone and dihydrotestosterone (DHT), are responsible for the normal growth and development of the male sex organs and for maintenance of secondary sex characteristics. These effects include the growth and maturation of prostate, seminal vesicles, penis and scrotum; the development of male hair distribution, such as facial, pubic, chest and axillary hair; laryngeal enlargement; vocal chord thickening; and alterations in body musculature and fat distribution. Testosterone and DHT are necessary for the normal development of secondary sex characteristics.

Male hypogonadism, a clinical syndrome resulting from insufficient secretion of testosterone, has two main etiologies. Primary hypogonadism is caused by defects of the gonads, such as Klinefelter's syndrome or Leydig cell aplasia, whereas secondary hypogonadism is the failure of the hypothalamus (or pituitary) to produce sufficient gonadotropins (FSH, LH).

12.2 Pharmacodynamics

No specific pharmacodynamic studies were conducted using AndroGel 1.62%.

12.3 Pharmacokinetics

Absorption

AndroGel 1.62% delivers physiologic amounts of testosterone, producing circulating testosterone concentrations that approximate normal levels (300 – 1000 ng/dL) seen in healthy men. AndroGel 1.62% provides continuous topical delivery of testosterone for 24 hours following once daily application to clean, dry, intact skin of the shoulders and upper arms. Average serum testosterone concentrations over 24 hours (Cavg) observed when AndroGel 1.62% was applied to the upper arms/shoulders were comparable to average serum testosterone concentrations (Cavg) when AndroGel 1.62% was applied using a rotation method utilizing the abdomen and upper arms/shoulders. The rotation of abdomen and upper arms/shoulders was a method used in the pivotal clinical trial [see Clinical Studies (14.1)].

Figure 2: Mean (±SD) Serum Total Testosterone Concentrations on Day 7 in Patients Following AndroGel 1.62% Once-Daily Application of 81 mg of Testosterone (N=33) for 7 Days

Distribution

Circulating testosterone is primarily bound in the serum to sex hormone-binding globulin (SHBG) and albumin. Approximately 40% of testosterone in plasma is bound to SHBG, 2% remains unbound (free) and the rest is loosely bound to albumin and other proteins.

Metabolism

Testosterone is metabolized to various 17-keto steroids through two different pathways. The major active metabolites of testosterone are estradiol and DHT.

Excretion

There is considerable variation in the half-life of testosterone concentration as reported in the literature, ranging from 10 to 100 minutes. About 90% of a dose of testosterone given intramuscularly is excreted in the urine as glucuronic acid and sulfuric acid conjugates of testosterone and its metabolites. About 6% of a dose is excreted in the feces, mostly in the unconjugated form. Inactivation of testosterone occurs primarily in the liver.

When AndroGel 1.62% treatment is discontinued, serum testosterone concentrations return to approximately baseline concentrations within 48-72 hours after administration of the last dose.

Potential for testosterone transfer

The potential for testosterone transfer following administration of AndroGel 1.62% when it was applied only to upper arms/shoulders was evaluated in two clinical studies of males dosed with AndroGel 1.62% and their untreated female partners. In one study, 8 male subjects applied a single dose of AndroGel 1.62% 81 mg to their shoulders and upper arms. Two (2) hours after application, female subjects rubbed their hands, wrists, arms, and shoulders to the application site of the male subjects for 15 minutes. Serum concentrations of testosterone were monitored in female subjects for 24 hours after contact occurred. After direct skin-to-skin contact with the site of application, mean testosterone Cavg and Cmax in female subjects increased by 280% and 267%, respectively, compared to mean baseline testosterone concentrations. In a second study evaluating transfer of testosterone, 12 male subjects applied a single dose of AndroGel 1.62% 81 mg to their shoulders and upper arms. Two (2) hours after application, female subjects rubbed their hands, wrists, arms, and shoulders to the application site of the male subjects for 15 minutes while the site of application was covered by a t-shirt. When a t-shirt was used to cover the site of application, mean testosterone Cavg and Cmax in female subjects increased by 6% and 11%, respectively, compared to mean baseline testosterone concentrations.

A separate study was conducted to evaluate the potential for testosterone transfer from 16 males dosed with AndroGel 1.62% 81 mg when it was applied to abdomen only for 7 days, a site of application not approved for AndroGel 1.62%. Two (2) hours after application to the males on each day, the female subjects rubbed their abdomens for 15 minutes to the abdomen of the males. The males had covered the application area with a T-shirt. The mean testosterone Cavg and Cmax in female subjects on day 1 increased by 43% and 47%, respectively, compared to mean baseline testosterone concentrations. The mean testosterone Cavg and Cmax in female subjects on day 7 increased by 60% and 58%, respectively, compared to mean baseline testosterone concentrations.

Effect of showering

In a randomized, 3-way (3 treatment periods without washout period) crossover study in 24 hypogonadal men, the effect of showering on testosterone exposure was assessed after once daily application of AndroGel 1.62% 81 mg to upper arms/shoulders for 7 days in each treatment period. On the 7th day of each treatment period, hypogonadal men took a shower with soap and water at either 2, 6, or 10 hours after drug application. The effect of showering at 2 or 6 hours post-dose on Day 7 resulted in 13% and 12% decreases in mean Cavg, respectively, compared to Day 6 when no shower was taken after drug application. Showering at 10 hours after drug application had no effect on bioavailability. The amount of testosterone remaining in the outer layers of the skin at the application site on the 7th day was assessed using a tape stripping procedure and was reduced by at least 80% after showering 2-10 hours post-dose compared to on the 6th day when no shower was taken after drug application.

Effect of hand washing

In a randomized, open-label, single-dose, 2-way crossover study in 16 healthy male subjects, the effect of hand washing on the amount of residual testosterone on the hands was evaluated. Subjects used their hands to apply the maximum dose (81 mg testosterone) of AndroGel 1.62% to their upper arms and shoulders. Within 1 minute of applying the gel, subjects either washed or did not wash their hands prior to study personnel wiping the subjects’ hands with ethanol dampened gauze pads. The gauze pads were then analyzed for residual testosterone content. A mean (SD) of 0.1 (0.04) mg of residual testosterone (0.12% of the actual applied dose of testosterone, and a 96% reduction compared to when hands were not washed) was recovered after washing hands with water and soap.

Effect of sunscreen or moisturizing lotion on absorption of testosterone

In a randomized, 3-way (3 treatment periods without washout period) crossover study in 18 hypogonadal males, the effect of applying a moisturizing lotion or a sunscreen on the absorption of testosterone was evaluated with the upper arms/shoulders as application sites. For 7 days, moisturizing lotion or sunscreen (SPF 50) was applied daily to the AndroGel 1.62% application site 1 hour after the application of AndroGel 1.62% 40.5 mg. Application of moisturizing lotion increased mean testosterone Cavg and Cmax by 14% and 17%, respectively, compared to AndroGel 1.62% administered alone. Application of sunscreen increased mean testosterone Cavg and Cmax by 8% and 13%, respectively, compared to AndroGel 1.62% applied alone.

13 NONCLINICAL TOXICOLOGY

13.1 Carcinogenesis, Mutagenesis, Impairment of Fertility

Carcinogenesis

Testosterone has been tested by subcutaneous injection and implantation in mice and rats. In mice, the implant induced cervical-uterine tumors which metastasized in some cases. There is suggestive evidence that injection of testosterone into some strains of female mice increases their susceptibility to hepatoma. Testosterone is also known to increase the number of tumors and decrease the degree of differentiation of chemically induced carcinomas of the liver in rats.

Mutagenesis

Testosterone was negative in the in vitro Ames and in the in vivo mouse micronucleus assays.

Impairment of Fertility

The administration of exogenous testosterone has been reported to suppress spermatogenesis in rats, dogs, and non-human primates, which was reversible on cessation of the treatment.

14 CLINICAL STUDIES

14.1 Clinical Trials in Hypogonadal Males

AndroGel 1.62% was evaluated in a multi-center, randomized, double-blind, parallel-group, placebo-controlled study (182-day double-blind period) in 274 hypogonadal men with body mass index (BMI) 18-40 kg/m^2 and 18-80 years of age (mean age 53.8 years). The patients had an average serum testosterone concentration of <300 ng/dL, as determined by two morning samples collected on the same visit. Patients were Caucasian 83%, Black 13%, Asian or Native American 4%. 7.5% of patients were Hispanic.

Patients were randomized to receive active treatment or placebo using a rotation method utilizing the abdomen and upper arms/shoulders for 182 days. All patients were started at a daily dose of 40.5 mg (two pump actuations) AndroGel 1.62% or matching placebo on Day 1 of the study. Patients returned to the clinic on Day 14, Day 28, and Day 42 for predose serum total testosterone assessments. The patient's daily dose was titrated up or down in 20.25 mg increments if the predose serum testosterone value was outside the range of 350-750 ng/dL. The study included four active AndroGel 1.62% doses: 20.25 mg, 40.5 mg, 60.75 mg, and 81 mg daily.

The primary endpoint was the percentage of patients with Cavg within the normal range of 300-1000 ng/dL on Day 112. In patients treated with AndroGel 1.62%, 81.6% (146/179) had Cavg within the normal range at Day 112. The secondary endpoint was the percentage of patients, with Cmax above three pre-determined limits. The percentages of patients with Cmax greater than 1500 ng/dL, and between 1800 and 2499 ng/dL on Day 112 were 11.2% and 5.5%, respectively. Two patients had a Cmax >2500 ng/dL on Day 112 (2510 ng/dL and 2550 ng/dL, respectively); neither of these 2 patients demonstrated an abnormal Cmax on prior or subsequent assessments at the same dose.

Patients could agree to continue in an open-label, active treatment maintenance period of the study for an additional 182 days.

Dose titrations on Days 14, 28, and 42 resulted in final doses of 20.25 mg – 81 mg on Day 112 as shown in Table 6.

Table 6: Mean (SD) Testosterone Concentrations (Cavg and Cmax) by final dose on Days 112 and 364
Parameter | Final Dose on Day 112
 | Placebo (n=27) | 20.25 mg (n=12) | 40.5 mg (n=34) | 60.75 mg (n=54) | 81 mg (n=79) | All Active (n=179)
Cavg (ng/dL) | 303 (135) | 457 (275) | 524 (228) | 643 (285) | 537 (240) | 561 (259)
Cmax (ng/dL) | 450 (349) | 663 (473) | 798 (439) | 958 (497) | 813 (479) | 845 (480)
 | Final Dose on Day 364
 |  | 20.25 mg (n=7) | 40.5 mg (n=26) | 60.75 mg (n=29) | 81 mg (n=74) | Continuing Active (n=136)
Cavg (ng/dL) |  | 386 (130) | 474 (176) | 513 (222) | 432 (186) | 455 (192)
Cmax (ng/dL) |  | 562 (187) | 715 (306) | 839 (568) | 649 (329) | 697 (389)

Figure 3 summarizes the pharmacokinetic profile of total testosterone in patients completing 112 days of AndroGel 1.62% treatment administered as a starting dose of 40.5 mg of testosterone (2 pump actuations) for the initial 14 days followed by possible titration according to the follow-up testosterone measurements.

Figure 3: Mean (±SD) Steady-State Serum Total Testosterone Concentrations on Day 112

Efficacy was maintained in the group of men that received AndroGel 1.62% for one full year. In that group, 78% (106/136) had average serum testosterone concentrations in the normal range at Day 364. Figure 4 summarizes the mean total testosterone profile for these patients on Day 364.

Figure 4: Mean (±SD) Steady-State Serum Total Testosterone Concentrations on Day 364

The mean estradiol and DHT concentration profiles paralleled the changes observed in testosterone. The levels of LH and FSH decreased with testosterone treatment. The decreases in levels of LH and FSH are consistent with reports published in the literature of long-term treatment with testosterone.

16 HOW SUPPLIED/STORAGE AND HANDLING

AndroGel 1.62% is supplied in non-aerosol, metered-dose pumps that deliver 20.25 mg of testosterone per complete pump actuation. The pumps are composed of plastic and stainless steel and an LDPE/aluminum foil inner liner encased in rigid plastic with a polypropylene cap. Each 88 g metered-dose pump is capable of dispensing 75 g of gel or 60-metered pump actuations; each pump actuation dispenses 1.25 g of gel.

AndroGel 1.62% is also supplied in unit-dose aluminum foil packets in cartons of 30. Each packet of 1.25 g or 2.5 g gel contains 20.25 mg or 40.5 mg testosterone, respectively.

NDC Number | Package Size
17139-562-88 | 88 g pump (each pump dispenses 60 metered pump actuations with each pump actuation containing 20.25 mg of testosterone in 1.25 g of gel)
17139-562-12 | Each unit dose packet contains 20.25 mg of testosterone provided in 1.25 g of gel
17139-562-31 | 30 packets (each unit dose packet contains 20.25 mg of testosterone provided in 1.25 g of gel)
17139-562-01 | Each unit dose packet contains 40.5 mg of testosterone provided in 2.5 g of gel
17139-562-30 | 30 packets (each unit dose packet contains 40.5 mg of testosterone provided in 2.5 g of gel)

Store at controlled room temperature 20°-25°C (68°-77°F); excursions permitted to 15°C to 30°C (59°- 86°F) [see USP Controlled Room Temperature].

Used AndroGel 1.62% pumps or used AndroGel 1.62% packets should be discarded in household trash in a manner that prevents accidental application or ingestion by children or pets.

17 PATIENT COUNSELING INFORMATION

Advise the patient to read the FDA-approved patient labeling (Medication Guide).

Patients should be informed of the following:

17.1 Use in Men with Known or Suspected Prostate or Breast Cancer

Men with known or suspected prostate or breast cancer should not use AndroGel 1.62% [see Contraindications (4) and Warnings and Precautions (5.4)].

17.2 Potential for Secondary Exposure to Testosterone and Steps to Prevent Secondary Exposure

Secondary exposure to testosterone in children and women can occur with the use of testosterone gel in men [see Warnings and Precautions (5.1)]. Cases of secondary exposure to testosterone have been reported in children.

Physicians should advise patients of the reported signs and symptoms of secondary exposure, which may include the following:

- In children: unexpected sexual development including inappropriate enlargement of the penis or clitoris, premature development of pubic hair, increased erections, and aggressive behavior.
- In women: changes in hair distribution, increase in acne, or other signs of testosterone effects.
- The possibility of secondary exposure to testosterone gel should be brought to the attention of a healthcare provider.
- AndroGel 1.62% should be promptly discontinued until the cause of virilization is identified.

Strict adherence to the following precautions is advised to minimize the potential for secondary exposure to testosterone from AndroGel 1.62% in men [see Medication Guide]:

- Children and women should avoid contact with unwashed or unclothed application site(s) of men using AndroGel 1.62%.
- Patients using AndroGel 1.62% should apply the product as directed and strictly adhere to the following:
  ○ Wash hands with soap and water immediately after application.
  ○ Cover the application site(s) with clothing after the gel has dried.
  ○ Wash the application site(s) thoroughly with soap and water prior to any situation where skin-to-skin contact of the application site with another person is anticipated.
- In the event that unwashed or unclothed skin to which AndroGel 1.62% has been applied comes in contact with the skin of another person, the general area of contact on the other person should be washed with soap and water as soon as possible [see Dosage and Administration (2.2), Warnings and Precautions (5.1) and Clinical Pharmacology (12.3)].

17.3 Potential for Venous Thromboembolism

Inform patients that AndroGel 1.62% can cause venous thromboembolism. Advise patients of the signs and symptoms of venous thromboembolism, which may include the following: lower limb pain, edema, or erythema; and dyspnea or chest pain. Advise patients to promptly report the signs and symptoms of venous thromboembolism, discontinue use of AndroGel 1.62%, and seek urgent medical care.

17.4 Potential for Increase in Blood Pressure

Inform patients that AndroGel 1.62% can increase BP which can increase cardiovascular risk over time. Instruct patients about the importance of monitoring BP periodically while on Androgel 1.62%. If BP increases while on AndroGel 1.62%, antihypertensive medications may need to be started, added, or adjusted to control BP, or AndroGel 1.62% may need to be discontinued.

17.5 Potential Adverse Reactions with Androgens

Patients should be informed that treatment with androgens may lead to adverse reactions which include:

- Changes in urinary habits such as increased urination at night, trouble starting the urine stream, passing urine many times during the day, having an urge to go to the bathroom right away, having a urine accident, being unable to pass urine and weak urine flow.
- Breathing disturbances, including those associated with sleep, or excessive daytime sleepiness.
- Too frequent or persistent erections of the penis.
- Nausea, vomiting, changes in skin color, or ankle swelling.

17.6 Patients Should Be Advised of the Following Instructions for Use

- Read the Medication Guide before starting AndroGel 1.62% therapy and to reread it each time the prescription is renewed.
- AndroGel 1.62% should be applied and used appropriately to maximize the benefits and to minimize the risk of secondary exposure in children and women.
- Keep AndroGel 1.62% out of the reach of children.
- AndroGel 1.62% is an alcohol based product and is flammable; therefore avoid fire, flame or smoking until the gel has dried.
- It is important to adhere to all recommended monitoring.
- Report any changes in their state of health, such as changes in urinary habits, breathing, sleep, and mood.
- AndroGel 1.62% is prescribed to meet the patient's specific needs; therefore, the patient should never share AndroGel 1.62% with anyone.
- Wait 2 hours before swimming or washing following application of AndroGel 1.62%. This will ensure that the greatest amount of AndroGel 1.62% is absorbed into their system.

Marketed by:

ASCEND Therapeutics US, LLC
Bridgewater, NJ 08807, USA 1-877-204-1013

© 2025 ASCEND Therapeutics US, LLC 2025AG0003

MEDICATION GUIDE
ANDROGEL® (AN DROW JEL) CIII
(testosterone gel) 1.62% for topical use

What is the most important information I should know about ANDROGEL 1.62%?
1. ANDROGEL 1.62% can transfer from your body to others including, children and women. Children and women should avoid contact with the unwashed or not covered (unclothed) areas where ANDROGEL 1.62% has been applied to your skin. Early signs and symptoms of puberty have occurred in young children who have come in direct contact with testosterone by touching areas where men have used ANDROGEL 1.62%.
Children
Signs and symptoms of early puberty in a child when they come in direct contact with ANDROGEL 1.62% may include:
Abnormal sexual changes:

- enlarged penis or clitoris.
- early growth of hair near the vagina or around the penis (pubic hair).
- erections or acting out sexual urges (sex drive).

Behavior problems:

- acting aggressively, behaving in an angry or violent way.

Women
Signs and symptoms in women when they come in direct contact with ANDROGEL 1.62% may include:

- changes in body hair.
- an abnormal increase in pimples (acne).

Stop using ANDROGEL 1.62% and call your healthcare provider right away if you see any signs and symptoms in a child or a woman that may have happened through accidental touching of the area where you have applied ANDROGEL 1.62%.
2. To lower the risk of transfer of ANDROGEL 1.62% from your body to others, follow these important instructions:

- Apply ANDROGEL 1.62% only to your shoulders and upper arms that will be covered by a short sleeve t-shirt.
- Wash your hands right away with soap and water after applying ANDROGEL 1.62%.
- After the gel has dried, cover the application area with clothing. Keep the area covered until you have washed the application area well or have showered.
- If you expect to have skin-to-skin contact with another person, first wash the application area well with soap and water.
- If a child or woman touches the area where you have applied ANDROGEL 1.62%, that area on the child or woman should be washed well with soap and water right away.

What is ANDROGEL 1.62%?
ANDROGEL 1.62% is a prescription medicine that contains testosterone. ANDROGEL 1.62% is used to treat adult males who have low or no testosterone due to certain medical conditions.

- Your healthcare provider will test your blood before you start and while you are using ANDROGEL 1.62%.
- It is not known if ANDROGEL 1.62% is safe or effective to treat men who have low testosterone due to aging.
- It is not known if ANDROGEL 1.62% is safe or effective in children younger than 18 years old. Improper use of ANDROGEL 1.62% may affect bone growth in children.

ANDROGEL 1.62% is a controlled substance (CIII) because it contains testosterone that can be a target for people who abuse prescription medicines. Keep your ANDROGEL 1.62% in a safe place to protect it. Never give your ANDROGEL 1.62% to anyone else, even if they have the same symptoms you have. Selling or giving away this medicine may harm others and is against the law.
ANDROGEL 1.62% is not meant for use in women.

Do not use ANDROGEL 1.62% if you:

- have breast cancer.
- have or might have prostate cancer.
- are pregnant. ANDROGEL 1.62% may harm your unborn baby.
- Women who are pregnant should avoid contact with the area of skin where ANDROGEL 1.62% has been applied.

Before using ANDROGEL 1.62%, tell your healthcare provider about all of your medical conditions, including if you:

- have breast cancer.
- have or might have prostate cancer.
- have urinary problems due to an enlarged prostate.
- have heart problems.
- have high blood pressure or are being treated for high blood pressure.
- have kidney or liver problems.
- have problems breathing while you sleep (sleep apnea).

Tell your healthcare provider about all the medicines you take, including prescription and over-the-counter medicines, vitamins, and herbal supplements. Using ANDROGEL 1.62% with certain other medicines can affect each other.
Especially, tell your healthcare provider if you take:

- insulin
- medicines that decrease blood clotting (blood thinners)
- corticosteroids

How should I use ANDROGEL 1.62%?

- See the detailed Instructions for Use about how to use ANDROGEL 1.62% at the end of this Medication Guide.
- It is important that you apply ANDROGEL 1.62% exactly as your healthcare provider tells you to.
- Your healthcare provider may change your ANDROGEL 1.62% dose. Do not change your ANDROGEL 1.62% dose without talking to your healthcare provider.
- Apply ANDROGEL 1.62% at the same time each morning. ANDROGEL 1.62% should be applied after showering or bathing.

What are the possible side effects of ANDROGEL 1.62%?
ANDROGEL 1.62% can cause serious side effects including:
See “What is the most important information I should know about ANDROGEL 1.62%?”

- If you already have enlargement of your prostate gland your signs and symptoms can get worse while using ANDROGEL 1.62%. This can include:
  ○ increased urination at night.
  ○ trouble starting your urine stream.
  ○ having to pass urine many times during the day.
  ○ having an urge to go to the bathroom right away.
  ○ having a urine accident.
  ○ being unable to pass urine or weak urine flow.
- Possible increased risk of prostate cancer. Your healthcare provider should check you for prostate cancer or any other prostate problems before you start and while you use ANDROGEL 1.62%.
- Blood clots in the legs or lungs. Signs and symptoms of a blood clot in your leg can include leg pain, swelling, or redness. Signs and symptoms of a blood clot in your lungs can include difficulty breathing or chest pain.
- Increase in blood pressure. AndroGel 1.62% can increase your blood pressure. Increases in blood pressure can increase the risk of heart attack or stroke over time. If your blood pressure increases while on AndroGel 1.62%, blood pressure medicines may need to be started. If you are taking blood pressure medicines, new blood pressure medicines may need to be added or your current blood pressure medicines may need to be adjusted to control your blood pressure. If your blood pressure cannot be controlled, AndroGel 1.62% may need to be stopped. Your healthcare provider will monitor your blood pressure while you are being treated with AndroGel 1.62%.
- In large doses ANDROGEL 1.62% may lower your sperm count.
- Swelling of your ankles, feet, or body, with or without heart failure.
- Enlarged or painful breasts.
- Have problems breathing while you sleep (sleep apnea).

Call your healthcare provider right away if you have any of the serious side effects listed above.
The most common side effects of ANDROGEL 1.62% include:

- increased prostate specific antigen (a test used to screen for prostate cancer)
- mood swings
- hypertension
- increased red blood cell count
- skin irritation where ANDROGEL 1.62% is applied

Other side effects include more erections than are normal for you or erections that last a long time.
Tell your healthcare provider if you have any side effect that bothers you or that does not go away.
These are not all the possible side effects of ANDROGEL 1.62%. For more information, ask your healthcare provider or pharmacist.
Call your doctor for medical advice about side effects. You may report side effects to FDA at 1-800-FDA-1088.

General information about the safe and effective use of ANDROGEL 1.62%
Medicines are sometimes prescribed for purposes other than those listed in a Medication Guide. Do not use ANDROGEL 1.62% for a condition for which it was not prescribed. Do not give ANDROGEL 1.62% to other people, even if they have the same symptoms you have. It may harm them. You can ask your pharmacist or healthcare provider for information about ANDROGEL 1.62% that is written for health professionals.

What are the ingredients in ANDROGEL 1.62%?
Active ingredient: testosterone
Inactive ingredients: carbopol 980, ethyl alcohol, isopropyl myristate, purified water and sodium hydroxide.
Marketed by: ASCEND Therapeutics US, LLC, Bridgewater, NJ 08807, USA © 2025 ASCEND Therapeutics US, LLC

For more information about ANDROGEL 1.62%, call 1-877-204-1013 or go to www.androgel.com.

This Medication Guide has been approved by the U.S. Food and Drug Administration Revised: 07/2025

2025AG0003

PATIENT INFORMATION

INSTRUCTIONS FOR USE
ANDROGEL® (AN DROW JEL) CIII
(testosterone gel) 1.62%
for topical use

Read this Instructions for Use for ANDROGEL1.62% before you start using it and each time you get a refill. There may be new information. This leaflet does not take the place of talking to your healthcare provider about your medical condition or treatment.

Applying ANDROGEL 1.62%:

- ANDROGEL 1.62% comes in a pump or in packets.
- Before applying ANDROGEL 1.62% make sure that your shoulders and upper arms are clean, dry, and that there is no broken skin.
- ANDROGEL 1.62% is to be applied to the area of your shoulders and upper arms that will be covered by a short sleeve t-shirt (See Figure A). Do not apply ANDROGEL 1.62% to any other parts of your body such as your stomach area (abdomen), penis, scrotum, chest, armpits (axillae), or knees.

(Figure A)

If you are using ANDROGEL 1.62% pump:

- Before using a new bottle of ANDROGEL 1.62 % for the first time, you will need to remove the cap and then prime the pump. To prime the ANDROGEL 1.62% pump, slowly push the pump all the way down 3 times, over the sink drain. Do not use any ANDROGEL 1.62% that came out while priming. Wash it down the sink to avoid accidental exposure to others. Your ANDROGEL 1.62% pump is now ready to use.
- Remove the cap from the pump. Then, put the spout opening at the top of the pump where the medicine comes out over the palm of your hand and slowly push the pump all the way down. Apply ANDROGEL 1.62% to the application site. You may also apply ANDROGEL 1.62% directly to the application site. Your healthcare provider will tell you the number of times to press the pump for each dose.
- Wash your hands with soap and water right away.

Find Your Dose as Prescribed by Your Healthcare Provider |  | Application Method
1 pump | 20.25 mg | Apply 1 pump of ANDROGEL 1.62% to 1 upper arm and shoulder.
2 pumps | 40.5 mg | Apply 1 pump of ANDROGEL 1.62% to 1 upper arm and shoulder and then apply 1 pump of ANDROGEL 1.62% to the opposite upper arm and shoulder.
3 pumps | 60.75 mg | Apply 2 pumps of ANDROGEL 1.62% to 1 upper arm and shoulder and then apply 1 pump of ANDROGEL 1.62% to the opposite upper arm and shoulder.
4 pumps | 81 mg | Apply 2 pumps of ANDROGEL 1.62% to 1 upper arm and shoulder and then apply 2 pumps of ANDROGEL 1.62% to the opposite upper arm and shoulder.

If you are using ANDROGEL 1.62% packets:

- Tear open the packet completely at the dotted line. Squeeze from the bottom of the packet to the top.
- Squeeze all of the ANDROGEL 1.62% out of the packet into the palm of your hand.
- Apply ANDROGEL 1.62% to the application site. You may also apply ANDROGEL 1.62% directly to the application site.
- Let the application site dry completely before putting on a t-shirt.
- ANDROGEL 1.62% is flammable until dry. Let ANDROGEL 1.62% dry before smoking or going near an open flame.
- Avoid showering, swimming or bathing for at least 2 hours after you apply ANDROGEL 1.62%.
- Wash your hands right away with soap and water after applying ANDROGEL 1.62%.

Find Your Dose as Prescribed by Your Healthcare Provider |  | Application Method
One 20.25 mg packet | 20.25 mg | Apply 1 packet of ANDROGEL 1.62% to 1 upper arm and shoulder.
One 40.5 mg packet | 40.5 mg | Apply half of the 40.5 mg packet of ANDROGEL 1.62% to 1 upper arm and shoulder and then apply the remaining packet contents to the opposite upper arm and shoulder.
One 40.5 mg packet and one 20.25 mg packet | 60.75 mg | Apply one 40.5 mg packet of ANDROGEL 1.62% to 1 upper arm and shoulder and then apply one 20.25 mg packet of ANDROGEL 1.62% to the opposite upper arm and shoulder.
Two 40.5 mg packets | 81 mg | Apply one 40.5 mg packet of ANDROGEL 1.62% to 1 upper arm and shoulder and then apply one 40.5 mg packet of ANDROGEL 1.62% to the opposite upper arm and shoulder.

How should I store ANDROGEL 1.62%?

- Store ANDROGEL 1.62% at room temperature between 68ºF to 77ºF (20ºC to 25ºC).
- When it is time to throw away the pump or packets, safely throw away used ANDROGEL 1.62% in the household trash. Be careful to prevent accidental exposure of children or pets.
- Keep ANDROGEL 1.62% away from fire.

Keep ANDROGEL 1.62% and all medicines out of the reach of children.

This Instructions for Use has been approved by the U.S. Food and Drug Administration.
Revised: 11/2022

2025AG0003

AndroGel ® (testosterone gel) 1.62%

NDC 17139–562–88

Dispense the accompanying Medication Guide to each patient.

AndroGel® (testosterone gel) 1.62% CIII

20.25 mg of testosterone per pump actuation*

*Each actuation delivers 1.25 g of gel

For Topical Use Only

Topical testosterone products may have different doses, strengths, or application instructions that may result in different systemic exposure.

Rx ONLY

Multi-dose pump capable of dispensing 60 metered pump actuations.

Ascend Therapeutics